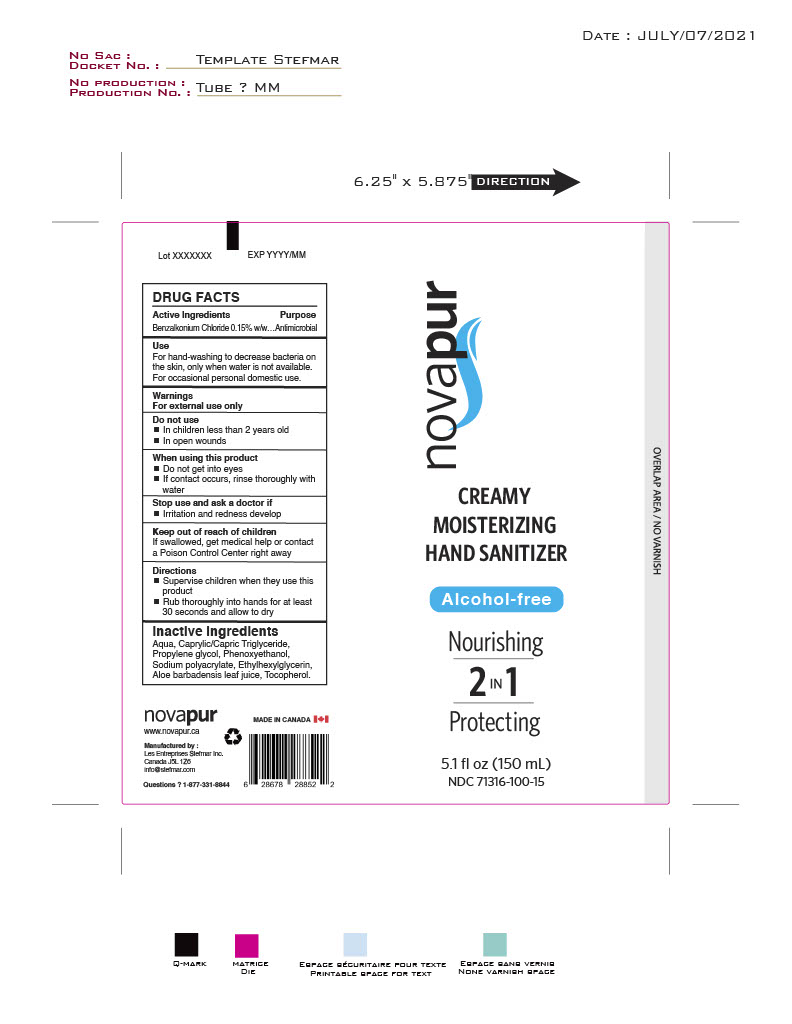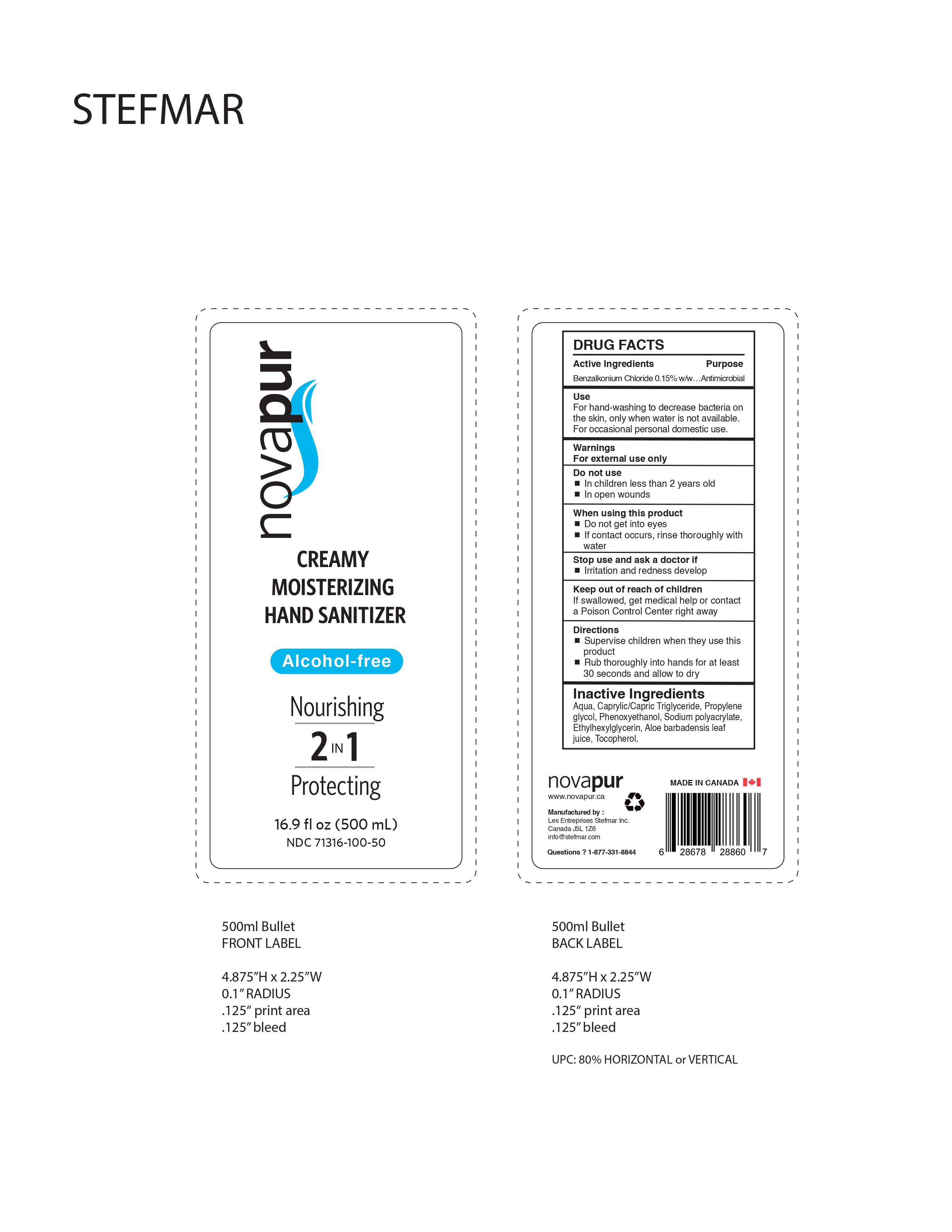 DRUG LABEL: Novapur Creamy Moisturizing Hand Sanitizer
NDC: 71316-100 | Form: GEL
Manufacturer: Les Entreprises Stefmar Inc
Category: otc | Type: HUMAN OTC DRUG LABEL
Date: 20210808

ACTIVE INGREDIENTS: BENZALKONIUM CHLORIDE 0.15 g/100 mL
INACTIVE INGREDIENTS: SODIUM POLYACRYLATE (8000 MW); MEDIUM-CHAIN TRIGLYCERIDES; WATER; ALOE VERA LEAF; .ALPHA.-TOCOPHEROL ACETATE, DL-; ETHYLHEXYLGLYCERIN; PROPYLENE GLYCOL; PHENOXYETHANOL

This is a hand sanitizer manufactured according to the Temporary Policy for Preparation of Certain Alcohol-Based Hand Sanitizer Products During the Public Health Emergency (CoViD-19); Guidance for Industry.

The hand sanitizer is manufactured using only the following United States Pharmacopoeia (USP) grade ingredients in the preparation of the product (percentage in final product formulation) consistent with World Health Organization (WHO) recommendations:

1. Alcohol (ethanol) (USP or Food Chemical Codex (FCC) grade) (80%, volume/volume (v/v)) in an aqueous solution denatured according to Alcohol and Tobacco Tax and Trade Bureau regulations in 27 CFR part 20.
2. Glycerol (1.45% v/v).
3. Hydrogen peroxide (0.125% v/v).
4. Sterile distilled water or boiled cold water.

The firm does not add other active or inactive ingredients. Different or additional ingredients may impact the quality and potency of the product.

Active Ingredient(s)

Benzalkonium Chloride 0.15% w/w

Purpose

Antimicrobial

Use

For hand-washing to decrease bacteria on the skin, only when water is not available. For occasional personal domestic use.

Warnings

For external use only.

Do not use

- in children less than 2 years old
- on open wounds

When using this product

- do not get into eyes.
- if contact occurs, rinse thoroughly with water.

.

Stop use and ask a doctor if

irritation and redness develops.

Keep out of reach of children. If swallowed, get medical help or contact a Poison Control Center right away.

Directions

- Supervise children when they use this product
- Rub thoroughly into hands for at least 30 seconds and allow to dry

Other information

- Store between 15-30C (59-86F)
- Avoid freezing and excessive heat above 40C (104F)

Inactive ingredients

Aqua, Caprylic/Capric Triglyceride, Propylene glycol, Phenoxyethanol, Sodium polyacrylate, Ethylhexylglycerin, Aloe barbadensis leaf juice, Tocopherol

Package Label - Principal Display Panel

500 mL NDC: 71316-100-50

150 mL NDC: 71316-100-15